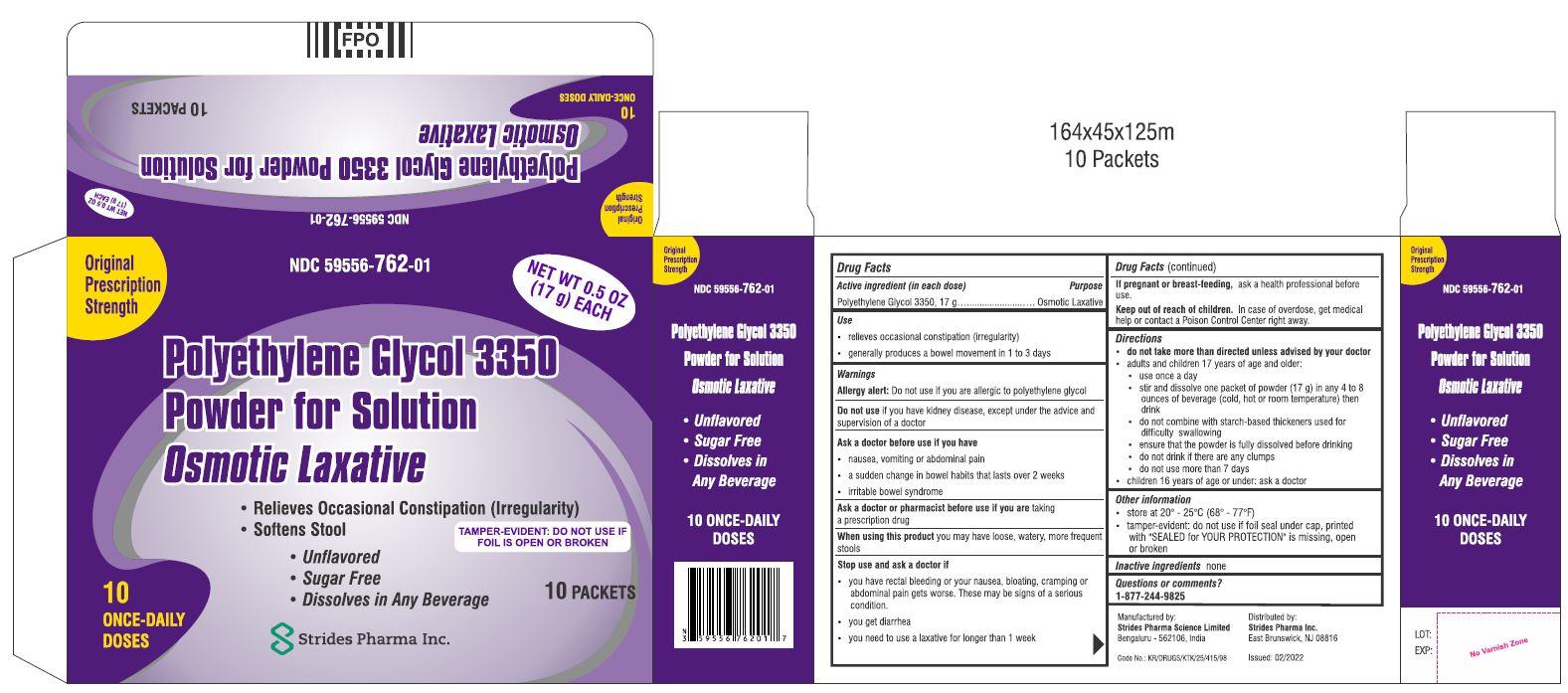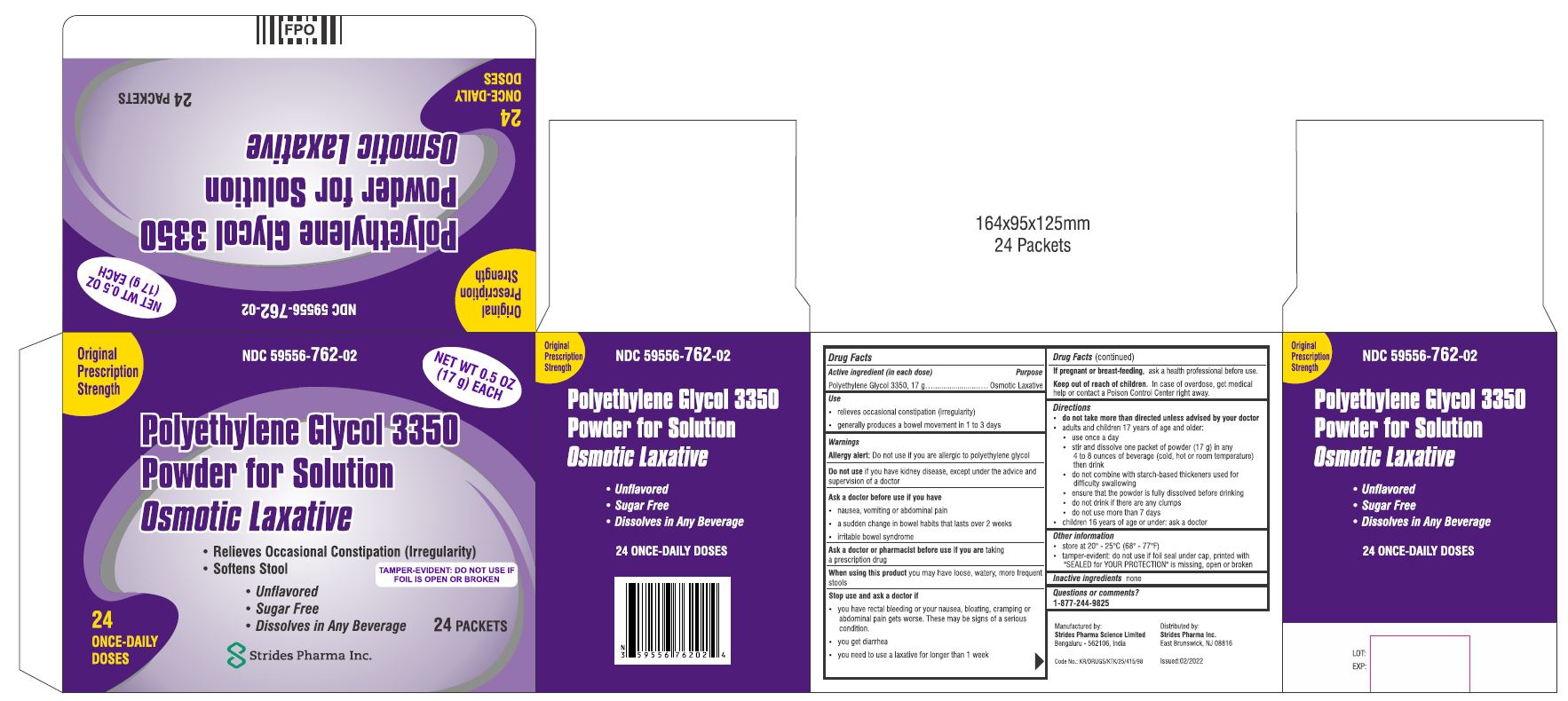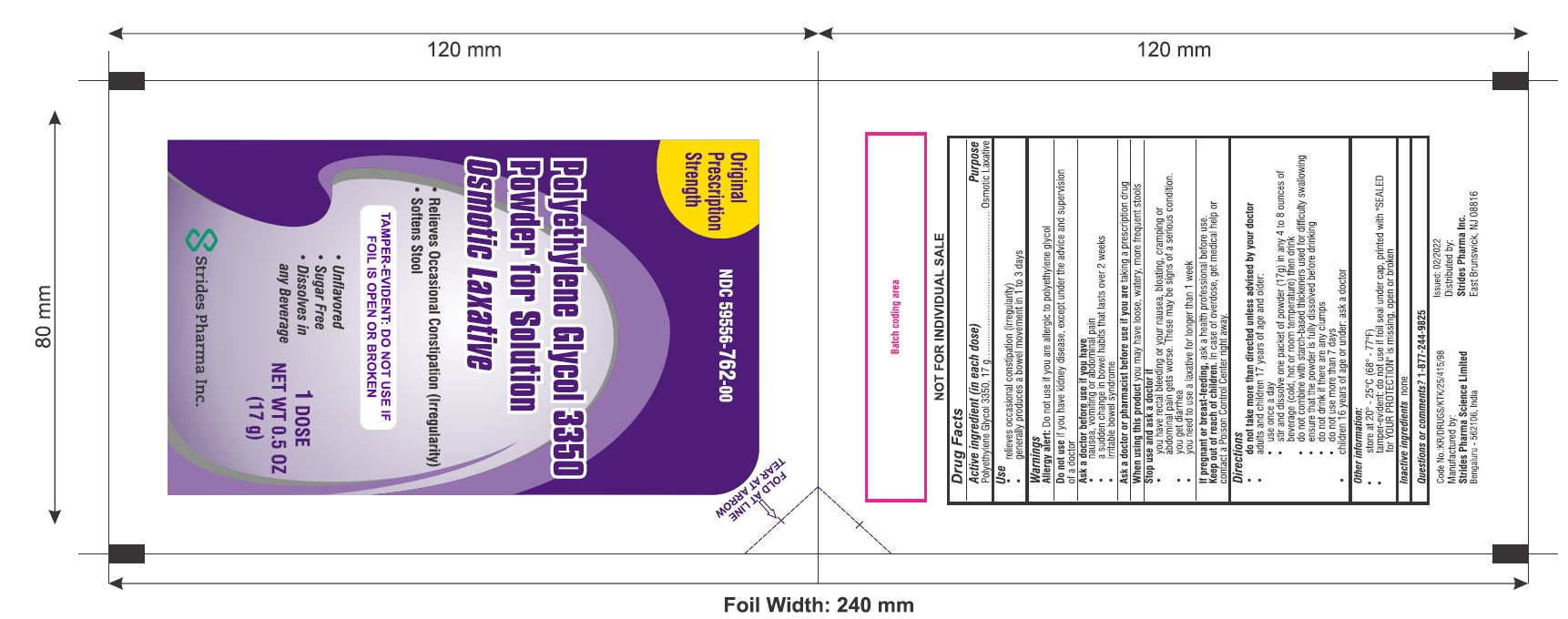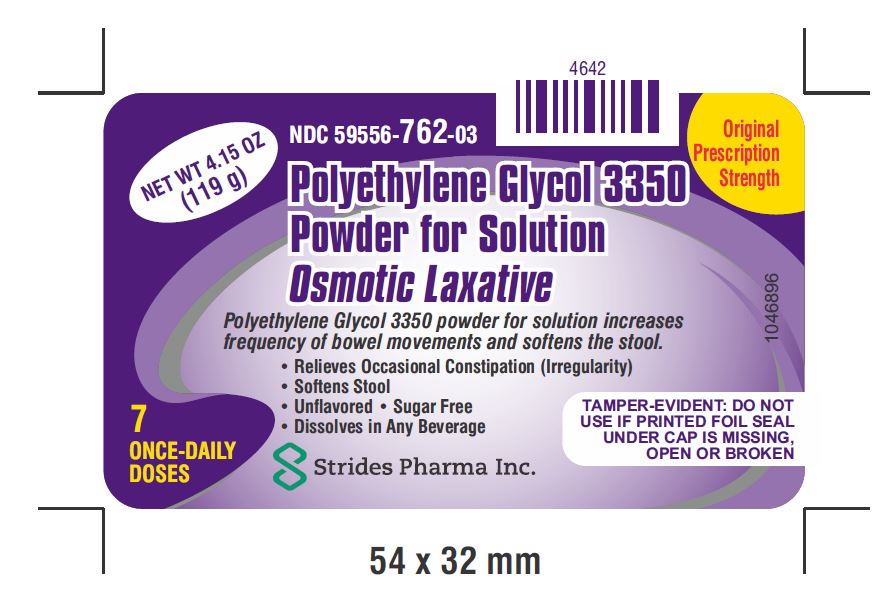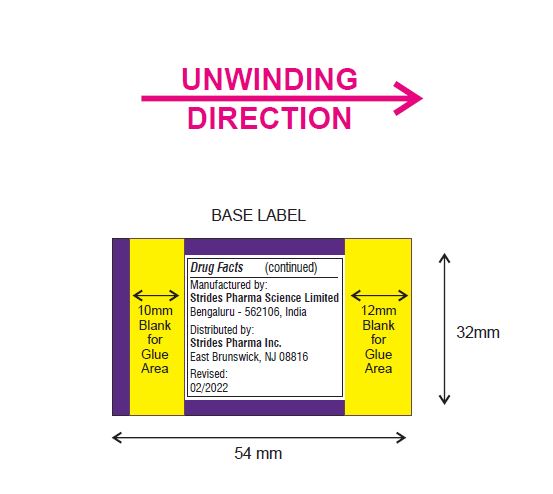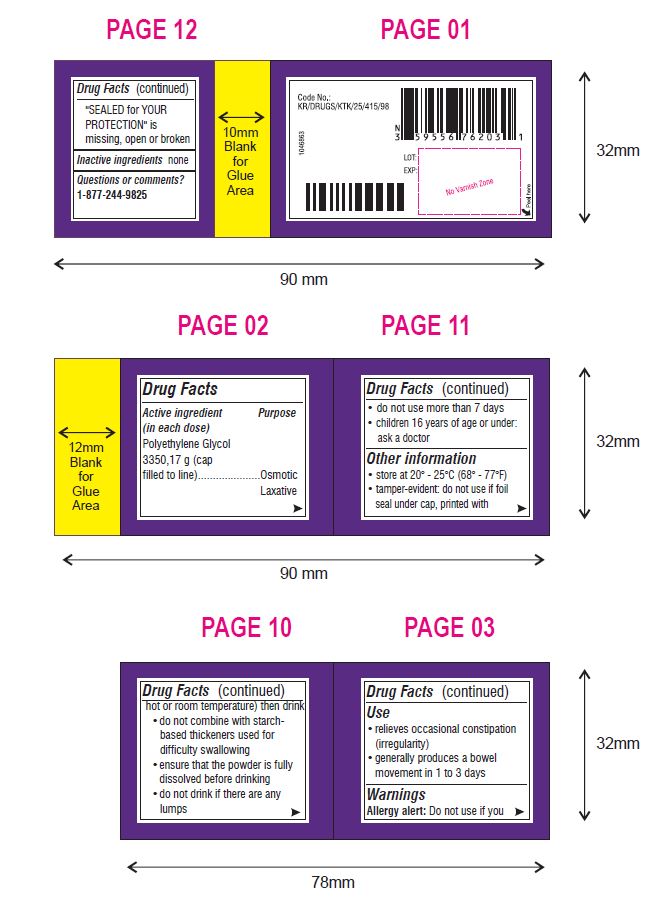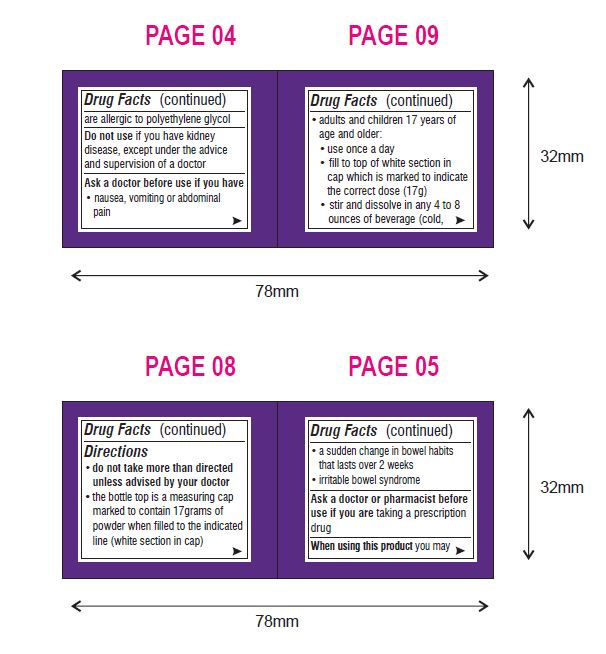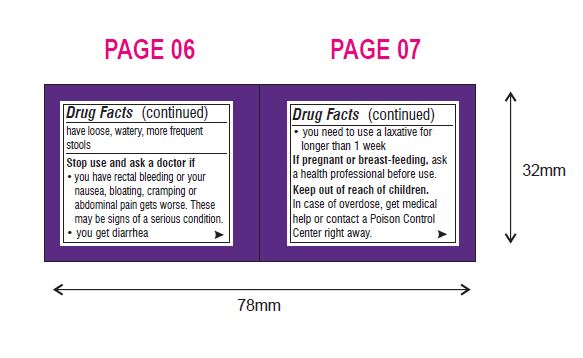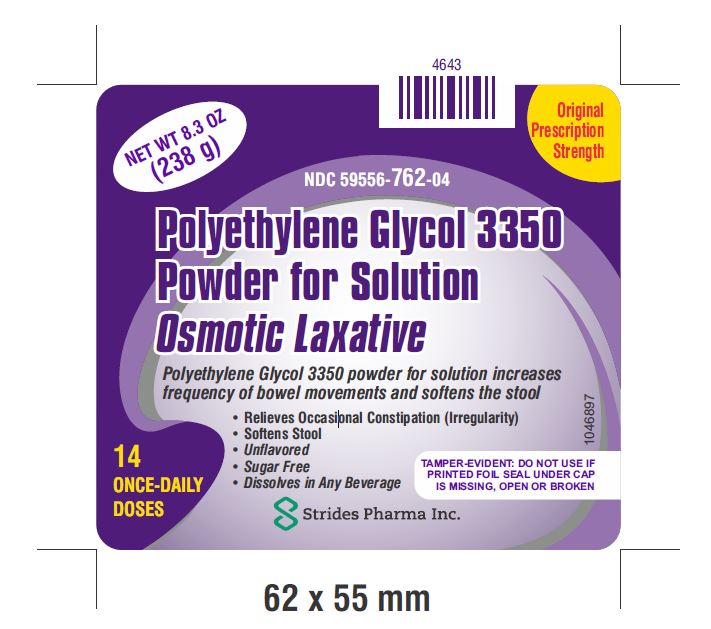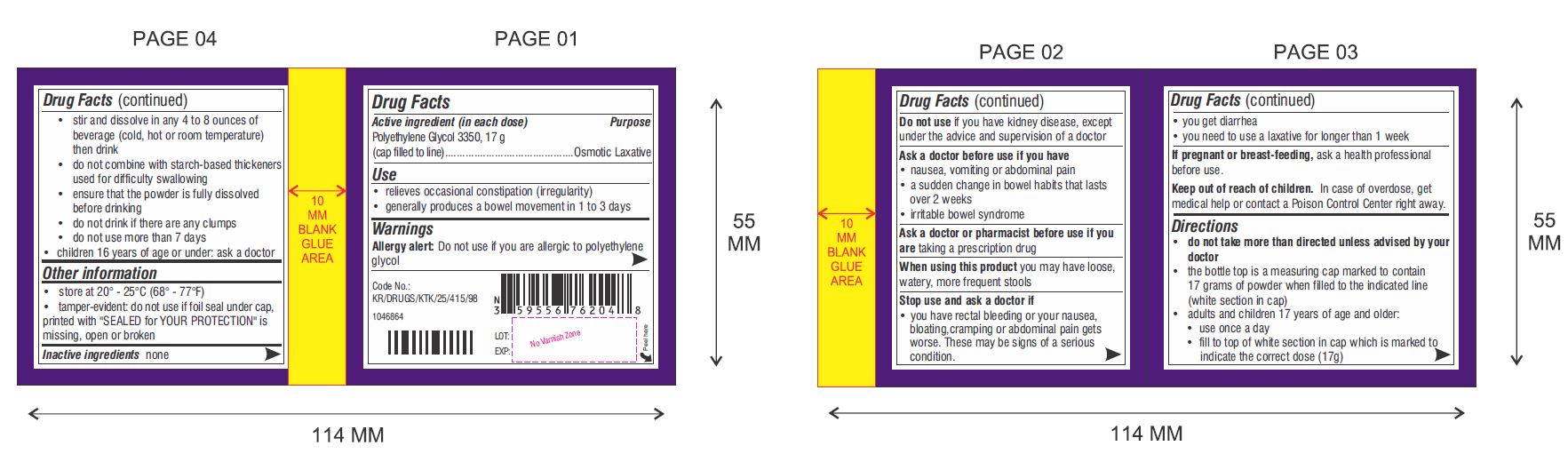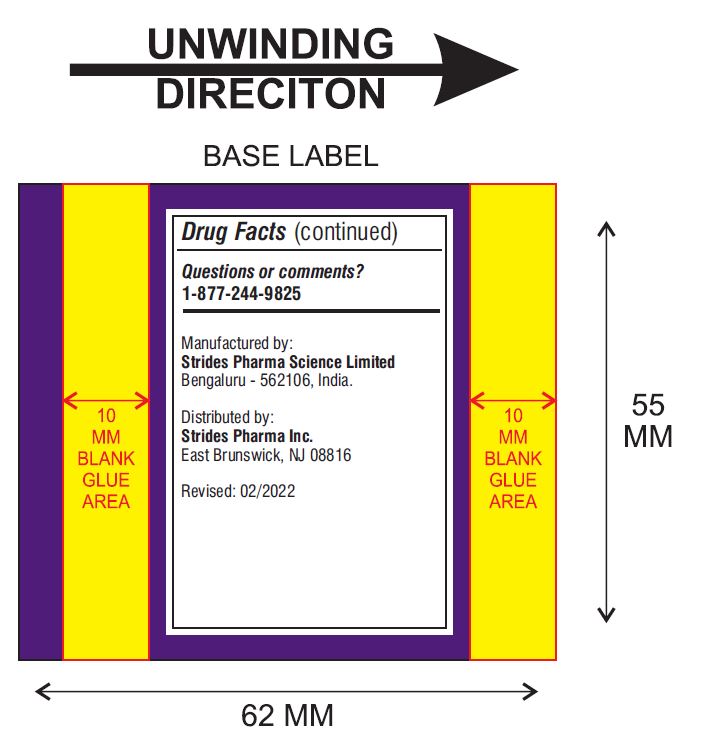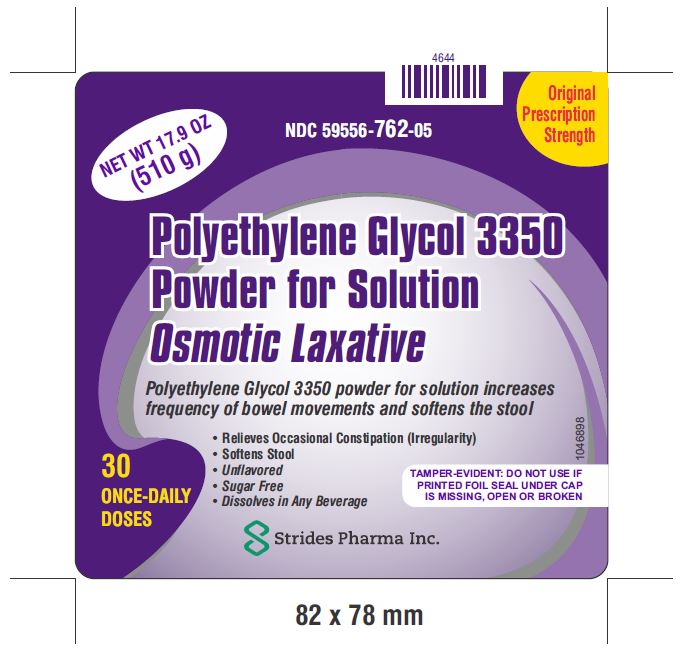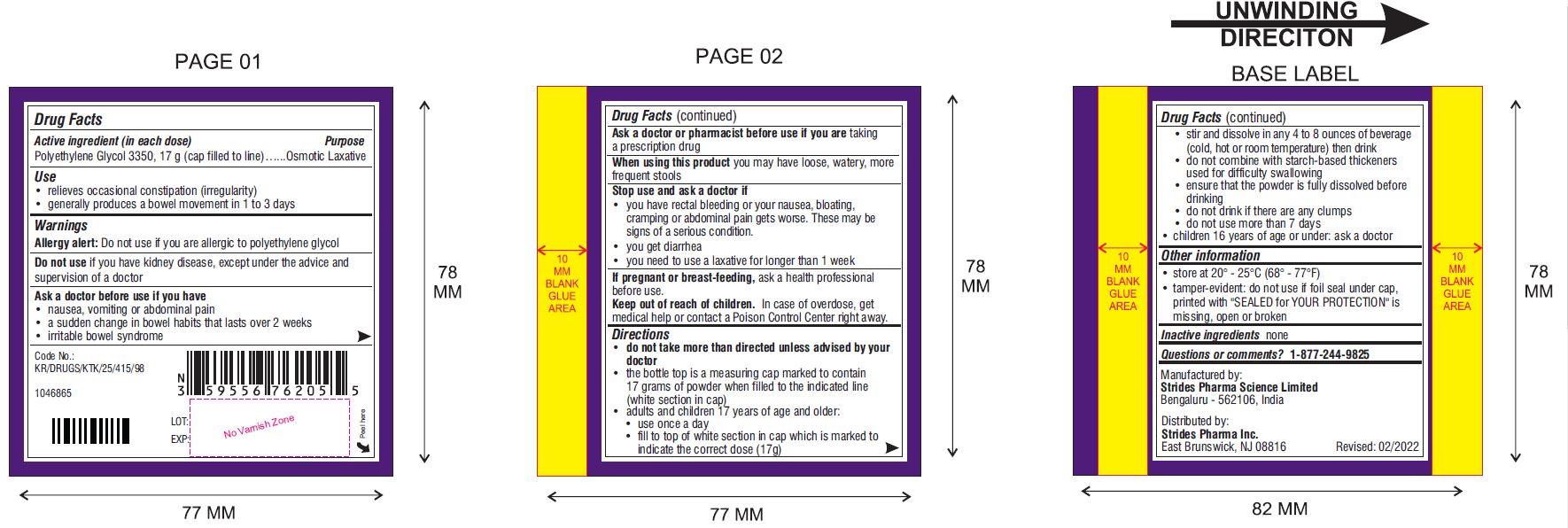 DRUG LABEL: Polyethylene Glycol 3350
NDC: 59556-762 | Form: POWDER, FOR SOLUTION
Manufacturer: Strides Pharma Inc
Category: otc | Type: HUMAN OTC DRUG LABEL
Date: 20220218

ACTIVE INGREDIENTS: Polyethylene Glycol 3350 17 g/17 g

Polyethelene Glycol 3350, Powder for Solution

Polyethylene Glycol 3350, Powder for Solution

Drug Facts

Active ingedient (in each dose) (Can only)

Polyethylene Glycol 3350, 17 g (cap filled to line)

Purpose

Osmotic Laxative

Active ingredient (in each dose) (Packet Only)

Polyethylene Glycol 3350, 17 g

Purpose

Osmotic Laxative

Use

- relieves occasional constipation (irregularity)
- generally produces a bowel movement in 1 to 3 days

Warnings

Allergy alert :

Do not use if you are allergic to polyethylene glycol

Do not use if you have kidney disease, except under the advice and supervision of a doctor

Ask a doctor before use if you have

- nausea, vomiting or abdominal pain
- a sudden change in bowel habits that lasts over 2 weeks
- irritable bowel syndrome

Ask a doctor or pharmacist before use if you are taking a prescription drug

When using this product you may have loose, watery, more frequent stools

Stop use and ask a doctor if

- you have rectal bleeding or your nausea, bloating, cramping or abdominal pain gets worse. These may be signs of a serious condition.
- you get diarrhea
- you need to use a laxative for longer than 1 week

PREGNANCY OR BREAST FEEDING

If pregnant or breast-feeding, ask a health professional before use.

KEEP OUT OF REACH OF CHILDREN

Keep out of the reach of children. In case of overdose, get medical help or contact a Poison Control Center right away.

Directions (Can Only)

- do not take more than directed unless advised by your doctor
- the bottle top is a measuring cap marked to contain 17 grams of powder when filled to the indicated line (white section in cap)
- adults and children 17 years of age and older:
  - use once a day
  - fill to top of white section in cap which is marked to indicate the correct dose (17 g)
  - stir and dissolve in any 4 to 8 ounces of beverage (cold, hot or room temperature) then drink
  - do not combine with starch-based thickeners used for difficulty swallowing
  - ensure that the powder is fully dissolved before drinking
  - do not drink if there are any clumps
  - do not use more than 7 days
- children 16 years of age or under: ask a doctor

Directions (Packet Only)

- do not take more than directed unless advised by your doctor
- adults and children 17 years of age and older:
  - use once a day
  - stir and dissolve one packet of powder (17 g) in any 4 to 8 ounces of beverage (cold, hot or room temperature) then drink
  - do not combine with starch-based thickeners used for difficulty swallowing
  - ensure that the powder is fully dissolved before drinking
  - do not drink if there are any clumps
  - do not use more than 7 days
- children 16 years of age or under: ask a doctor

Other Information

- store at 20° - 25°C (68° - 77°F)
- tamper-evident: do not use if foil seal under cap, printed with "SEALED for YOUR PROTECTION" is missing, open or broken

Inactive ingredients

none

Questions or comments?

1-877-244-9825

Polyethylene Glycol 3350 powder for solution increases frequency of bowel movements and softens the stool.

Manufactured by:

Strides Pharma Science Limited

Bengaluru – 5562106, India.

Distributed by

Strides Pharma Inc.

East Brunswick, NJ 08816

PACKAGE LABEL.PRINCIPAL DISPLAY PANEL

10

Packets

NDC 59556-762-01

Polyethylene Glycol 3350

Powder for Solution

Osmotic Laxative

- Relieves Occasional Constipation (Irregularity)
- Softens Stool

TAMPER-EVIDENT: DO NOT USE IF FOIL IS OPEN OR BROKEN

- Unflavored
- Sugar Free
- Dissolves in Any Beverage

10 ONCE-DAILY DOSES

10 PACKETS

NET WT 0.5 OZ (17g) EACH

10s carton

PACKAGE LABEL.PRINCIPAL DISPLAY PANEL

24

Packets

NDC 59556-762-02

Polyethylene Glycol 3350

Powder for Solution

Osmotic Laxative

- Relieves Occasional Constipation (Irregularity)
- Softens Stool

TAMPER-EVIDENT: DO NOT USE IF FOIL IS OPEN OR BROKEN

- Unflavored
- Sugar Free
- Dissolves in Any Beverage

24 ONCE-DAILY DOSES

24 PACKETS

NET WT 0.5 OZ (17g) EACH

24s carton

PACKAGE LABEL.PRINCIPAL DISPLAY PANEL

NDC 59556-762-00

Original

Prescription

Strength

Polyethylene Glycol 3350

Powder for Solution

Osmotic Laxative

- Relieves Occasional Constipation (Irregularity)
- Softens Stool

TAMPER-EVIDENT: DO NOT USE IF FOIL IS OPEN OR BROKEN

- Unflavored
- Sugar Free
- Dissolves in Any Beverage

1 DOSE

NET WT 0.5 OZ (17 g)

packet

PACKAGE LABEL.PRINCIPAL DISPLAY PANEL

NDC 59556-762-03

Original

Prescription

Strength

Polyethylene Glycol 3350

Powder for Solution

Osmotic Laxative

- Relieves Occasional Constipation (Irregularity)
- Softens Stool

TAMPER-EVIDENT: DO NOT USE IF PRINTED FOIL SEAL UNDER CAP IS MISSING, OPEN OR BROKEN

- Unflavored
- Sugar Free
- Dissolves in Any Beverage

7

ONCE-DAILY

DOSES

NET WT 4.15 OZ (119 g)

119 g CAN - FRONT
119 g BACK [CAN]
119g BACK [CAN]
119g BACK [CAN]
119g BACK [CAN]

PACKAGE LABEL.PRINCIPAL DISPLAY PANEL

NDC 59556-762-04

Original

Prescription

Strength

Polyethylene Glycol 3350

Powder for Solution

Osmotic Laxative

- Relieves Occasional Constipation (Irregularity)
- Softens Stool

TAMPER-EVIDENT: DO NOT USE IF PRINTED FOIL SEAL UNDER CAP IS MISSING, OPEN OR BROKEN

- Unflavored
- Sugar Free
- Dissolves in Any Beverage

14

ONCE-DAILY

DOSES

NET WT 8.3 OZ (238 g)

238 G CAN - FRONT
238 G CAN - BACK
238 G CAN - BACK

PACKAGE LABEL.PRINCIPAL DISPLAY PANEL

NDC 59556-762-05

Original

Prescription

Strength

Polyethylene Glycol 3350

Powder for Solution

Osmotic Laxative

- Relieves Occasional Constipation (Irregularity)
- Softens Stool

TAMPER-EVIDENT: DO NOT USE IF PRINTED FOIL SEAL UNDER CAP IS MISSING, OPEN OR BROKEN

- Unflavored
- Sugar Free
- Dissolves in Any Beverage

30

ONCE-DAILY

DOSES

NET WT 17.9 OZ (510 g)

510 g CAN - FRONT
510 g CAN - BACK